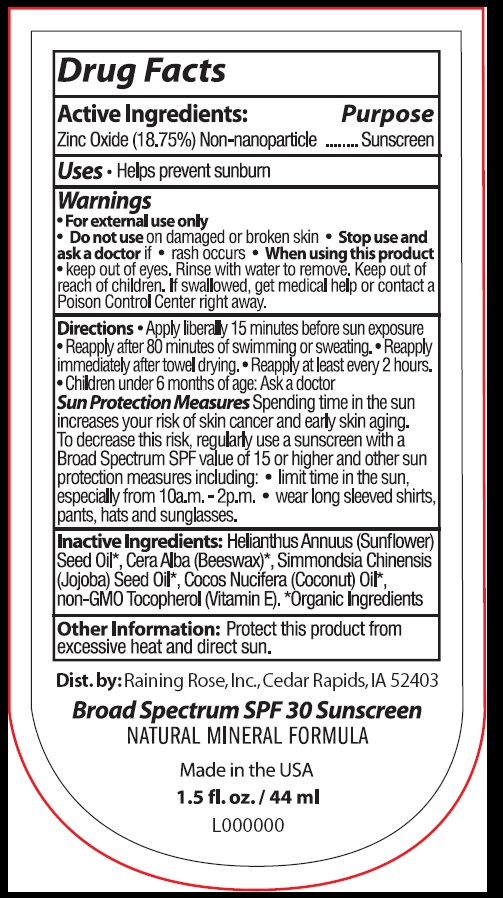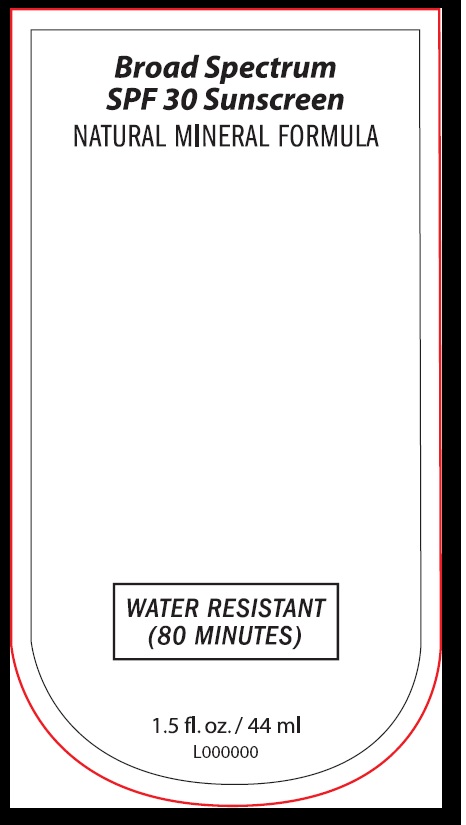 DRUG LABEL: Natural Mineral Formula
NDC: 65692-0738 | Form: LOTION
Manufacturer: Raining Rose, Inc.
Category: otc | Type: HUMAN OTC DRUG LABEL
Date: 20190821

ACTIVE INGREDIENTS: ZINC OXIDE 8.25 g/44 mL
INACTIVE INGREDIENTS: SUNFLOWER OIL; YELLOW WAX; JOJOBA OIL; COCONUT OIL; TOCOPHEROL

Broad Spectrum SPF 30 NATURAL MINERAL FORMULA

DRUG FACTS

Active Ingredients:

Zinc Oxide (18.75%) Non-nanoparticle

Purpose

Sunscreen

Uses

- Helps prevent sunburn

Warnings

- For External Use Only

- Do not use on damaged or broken skin

Stop use and as a doctor if • rash occurs

When using this product • Keep out of eyes. Rinse well with water to remove.

Keep out of reach of children.

If swallowed, get medical help or call a Poison Control Center right away.

DOSAGE AND ADMINISTRATION

Directions •Apply liberally 15 minutes before sun exposure
• Reapply after 80 minutes of swimming or sweating, •Reapply
• immediately after towel drying. •Reapply at least every 2 hours
• Children under 6 months of age: Ask a doctor
Sun Protection Measures Spending time in the sun increases your
risk of skin cancer and early skin aging. To decrease this risk, regularly
use a sunscreen with a Broad Spectrum SPF value of 15 or higher and
other protection measures including:
• limit time in the sun, especially from 10a.m. - 2p.m.
• wear long sleeved shirts, pants, hat, and sunglasses.

INACTIVE INGREDIENT

Inactive Ingredients: Helianthus Annus (Sunflower) Seed Oil*, Cera Alba (Beeswax)*,

Simmondsia Chinensia (Jojoba) Seed Oil*, Cocos Nucifera (Coconut) Oil*,

non-GMO Tocopherol (Vitamin E).

*Organic Ingredients

Other Information: Protect this product from excessive heart and direct sun.

Product Package Labeling

Dist. by: Raining Rose, Inc., Cedar Rapids, IA 52403

Broad Spectrum SPF 30 Sunscreen

NATURAL MINERAL FORMULA

WATER RESISTANT

(80 MINUTES)

1.5 fl. oz. / 44 ml

L000000

Dist. by: Raining Rose Inc., Cedar Rapids, IA 52403

Broad Spectrum SPF 30 Sunscreen

NATURAL MINERAL FORMULA

Made in the USA

1.5 fl. oz. / 44 ml

L000000

rege